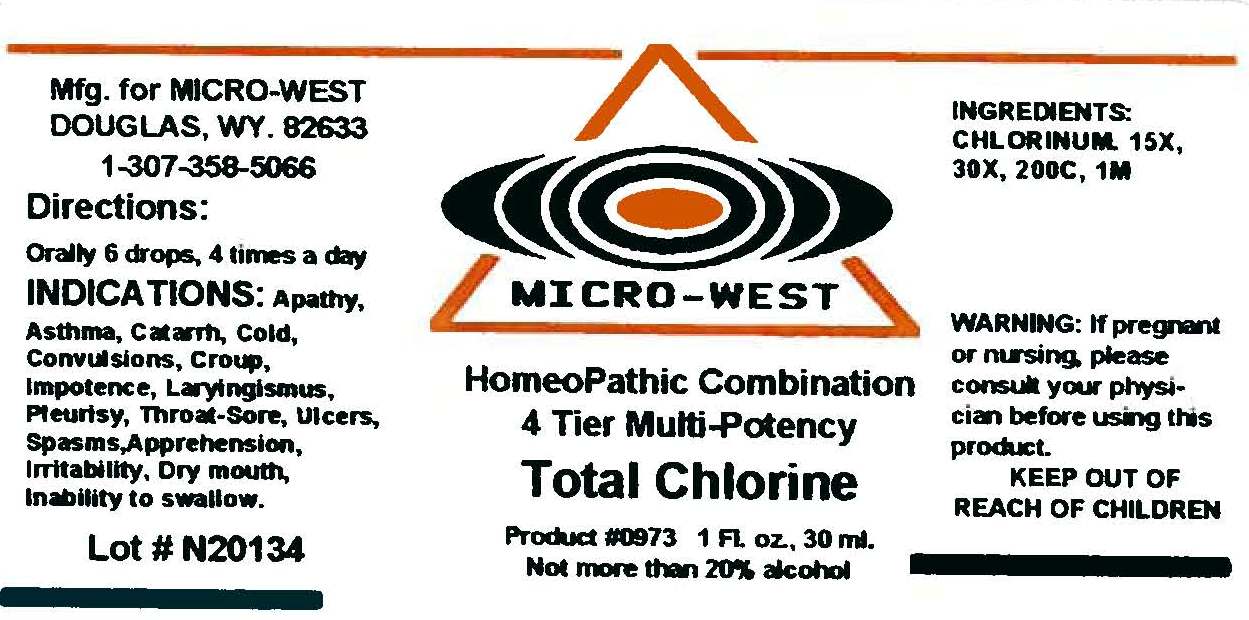 DRUG LABEL: Total Chlorine
NDC: 58836-0973 | Form: LIQUID
Manufacturer: White Manufacturing Incorporated
Category: homeopathic | Type: HUMAN OTC DRUG LABEL
Date: 20110815

ACTIVE INGREDIENTS: Chlorine 15 [hp_X]/30 mL
INACTIVE INGREDIENTS: Alcohol

DRUG FACTS

Active Ingredients

Chlorinum 15X, 30X, 200C, 1M

Uses

Apathy, Asthma, Catarrh, Cold,Convulsions,Croup, Impotence, Laryingismus, Pleurisy, Throat-sore, Ulcers, Spasms, Apprenhension, Irritability, Dry mouth, Inability to Swallow

Keep Out of Reach of Children

INDICATIONS

Indications:Apathy, Asthma, Catarrh, Cold, Convulsions, Croup, Impotence, Laryingismus, Pteurisy, Throat-Sore, Ulcers, Spasms, Apprension, Irritability, Dry Mouth, Inability to swallow

Ask Doctor

Warning: If pregnant or nursing, please consult physician before using this product

Directions

Orally, 6 drops, 4 times a day

INACTIVE INGREDIENT

not more than 20% alcohol

Principal display panel Total Chlorine

test image